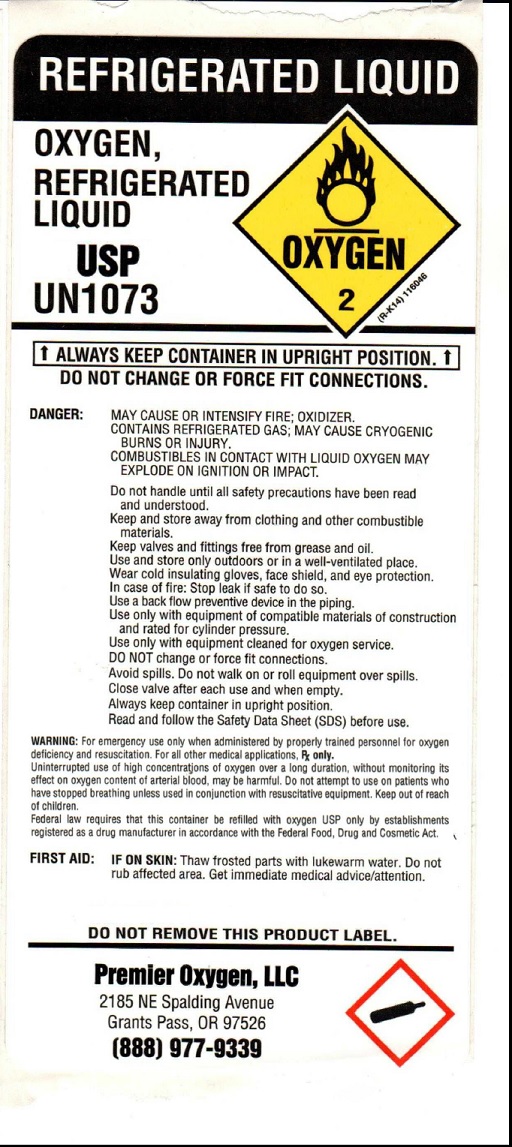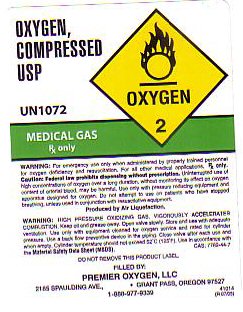 DRUG LABEL: Oxygen
NDC: 67932-1313 | Form: GAS
Manufacturer: Premier Oxygen LLC
Category: prescription | Type: HUMAN PRESCRIPTION DRUG LABEL
Date: 20251024

ACTIVE INGREDIENTS: OXYGEN 99.5 L/100 L

GENERAL WARNINGS AND PRECAUTIONS

WARNING: HIGH PRESSURE OXIDIZING GAS. VIGOROUSLY ACCELERATES COMBUSTION. KEEP OIL AND GREASE AWAY. OPEN VALVE SLOWLY. STORE AND USE WITH ADEQUATE VENTILATION. USE ONLY WITH EQUIPMENT CLEANED FOR OXYGEN SERVICE AND RATED FOR CYLINDER PRESSURE. USE A BACK FLOW PREVENTATIVE DEVICE IN THE PIPING. CLOSE VALVE AFTER EACH USE AND WHEN EMPTY. CYLINDER TEMPERATURE SHOULD NOT EXCEED 52 C (125 F). USE IN ACCORDANCE WITH THE MATERIAL SAFETY DATA SHEET. DO NOT REMOVE THIS PRODUCT LABEL.

OXYGEN COMPRESSED LABEL

OXYGEN COMPRESSED USP UN 1072 OXYGEN - 2 MEDICAL GAS Rx ONLY. WARNING: FOR EMERGENCY USE ONLY WHEN ADMINISTERED BY PROPERLY TRAINED PERSONNEL FOR OXYGEN DEFICIENCY AND RESUSCITATION. FOR ALL OTHER MEDICAL APPLICATIONS Rx ONLY. CAUTION FEDERAL LAW PROHIBITS DISPENSING WITHOUT PRESCRIPTION. UNINTERRUPTED USE OF HIGH CONCENTRATIONS OF OXYGEN OVER A LONG DURATION WITHOUT MONITORING ITS EFFECT ON OXYGEN CONCENTRATION OF ARTERIAL BLOOD MAY BE HARMFUL. USE ONLY WITH PRESSURE REDUCING EQUIPMENT AND APPARATUS DESIGNED FOR OXYGEN. DO NOT ATTEMPT TO USE ON PATIENTS WHO HAVE STOPPED BREATHING UNLESS USED IN CONJUNCTION WITH RESUSCITATIVE EQUIPMENT. PRODUCED BY AIR LIQUEFACTION

41014 (R07/05) CAS 7782-44-7

res

OXYGEN REFRIGERATED LIQUID LABEL

REFRIGERATED LIQUID
OXYGEN,
REFRIGERATED
LIQUID

USP
UN1073

OXYGEN
2
(R-K14) 116046

DANGER:ALWAYS KEEP CONTAINER IN UPRIGHT POSITION.
DO NOT CHANGE OR FORCE FIT CONNECTIONS.
MAY CAUSE OR INTENSIFY FIRE: OXIDIZER.
CONTAINS REFRIGERATED GAS; MAY CAUSE CRYOGENIC
BURNS OR INJURY.
COMBUSTIBLES IN CONTACT WITH LIQUID OXYGEN MAY
EXPLODE ON IGNITION OR IMPACT.

Do not handle until all safety precautions have been read
and understood.
Keep and store away from clothing and other combustible
materials.
Keep valves and fittings free from grease and oil.
Use and store only outdoors or in a well-ventilated place.
Wear cold insulating gloves, face shield, and eye protection.
In case of fire: Stop leak if safe to do so.
Use aback flow preventive device in the piping.
Use only with equipment of compatible materials of construction
and rated for cylinder pressure.
Use only with equipment cleaned for oxygen service.

DO NOTchange or force fit connections.
Avoid spills. Do not walk on or roll equipment over spills.
Close valve after each use and when empty.
Always keep container in upright position.
Read and follow the Safety DataSheet (SDS) before use.

WARNING:For emergency use only when administered by properly trained personnel for oxygen
deficiency and resuscitation. For all other medical applications. Rx only.
Uninterrupted use of high concentrations of oxygen over a long duration. without monitoring its
effect on oxygen content 01 arterial blood, may be harmful. Do not attempt to use on patients who
have stopped breathing unless used in conjunction with resuscitative equipment. Keep out of reach
of children.
Federal law requires that this container be refilled with oxygen USP only by establishments
registered as a drug manufacturer in accordance with the Federal Food, Drug and Cosmetic Act.

FIRSTAID: IF ON SKIN:Thaw frosted parts with lukewarm water. Do not
rub affected area. Get immediate medical advice/attention.

DO NOT REMOVE THIS PRODUCT LABEL.
Premier Oxygen, LLC
2185 NE Spalding Avenue
Grants Pass, OR 97526
(888) 977•9339

res